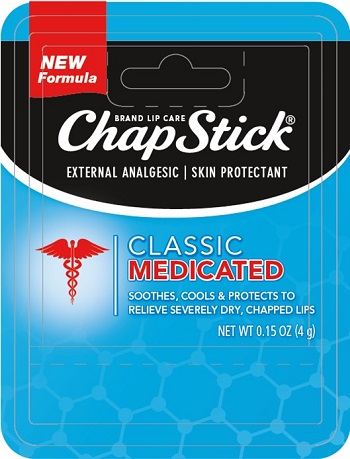 DRUG LABEL: CHAPSTICK CLASSIC MEDICATED
NDC: 0573-2031 | Form: STICK
Manufacturer: Haleon US Holdings LLC
Category: otc | Type: HUMAN OTC DRUG LABEL
Date: 20240123

ACTIVE INGREDIENTS: CAMPHOR (SYNTHETIC) 16 mg/1 g; MENTHOL, UNSPECIFIED FORM 6 mg/1 g; PETROLATUM 410 mg/1 g
INACTIVE INGREDIENTS: ARACHIDYL PROPIONATE; CETYL ALCOHOL; CARNAUBA WAX; ISOPROPYL MYRISTATE; LANOLIN; LIGHT MINERAL OIL; OCTYLDODECANOL; OLEYL ALCOHOL; PARAFFIN; PHENYL TRIMETHICONE; COCOA BUTTER; WHITE WAX

Drug Facts

Active ingredients

Camphor 1.6%

Menthol 0.6%

White Petrolatum 41%

Purposes

External analgesic

External analgesic

Skin protectant

Uses

- helps prevent and temporarily protects chafed, chapped or cracked lips
- temporary relief of pain associated with fever blisters and cold sores
- helps prevent and protect from the drying effects of wind and cold weather

Warnings

For external use only

When using this productavoid contact with the eyes.

Stop use and ask a doctor if

- condition worsens
- symptoms persist for more than 7 days or clear up and occur again within a few days

Keep out of reach of children.If swallowed, get medical help or contact a Poison Control Center right away.

Directions

- adults and children 2 years of age and older: apply to lips not more than 3 to 4 times daily
- children under 2 years of age: ask a doctor

Other information

- store at 20-25°C (68-77°F)

Inactive ingredients

arachidyl propionate, cetyl alcohol, carnauba wax, fragrance, isopropyl lanolate, isopropyl myristate, lanolin, light mineral oil, octyldodecanol, oleyl alcohol, paraffin, phenyl trimethicone, cocoa butter, white wax

Questions or comments?

call weekdays from 9 AM to 6 PM at 1-800-245-1040

Additional information

Distributed by: GSK CH, Warren, NJ 07059

For most recent product information, visit www.chapstick.com

Trademarks owned or licensed by GSK.

© 2022 GSK or licensor

Paraben Free

PRINCIPAL DISPLAY PANEL

NEW Formula

BRAND LIP CARE

ChapStick®

EXTERNAL ANALGESIC | SKIN PROTECTANT

CLASSIC
MEDICATED

SOOTHES, COOLS & PROTECTS TO
RELIEVE SEVERELY DRY, CHAPPED LIPS

NET WT 0.15 OZ (4 g)